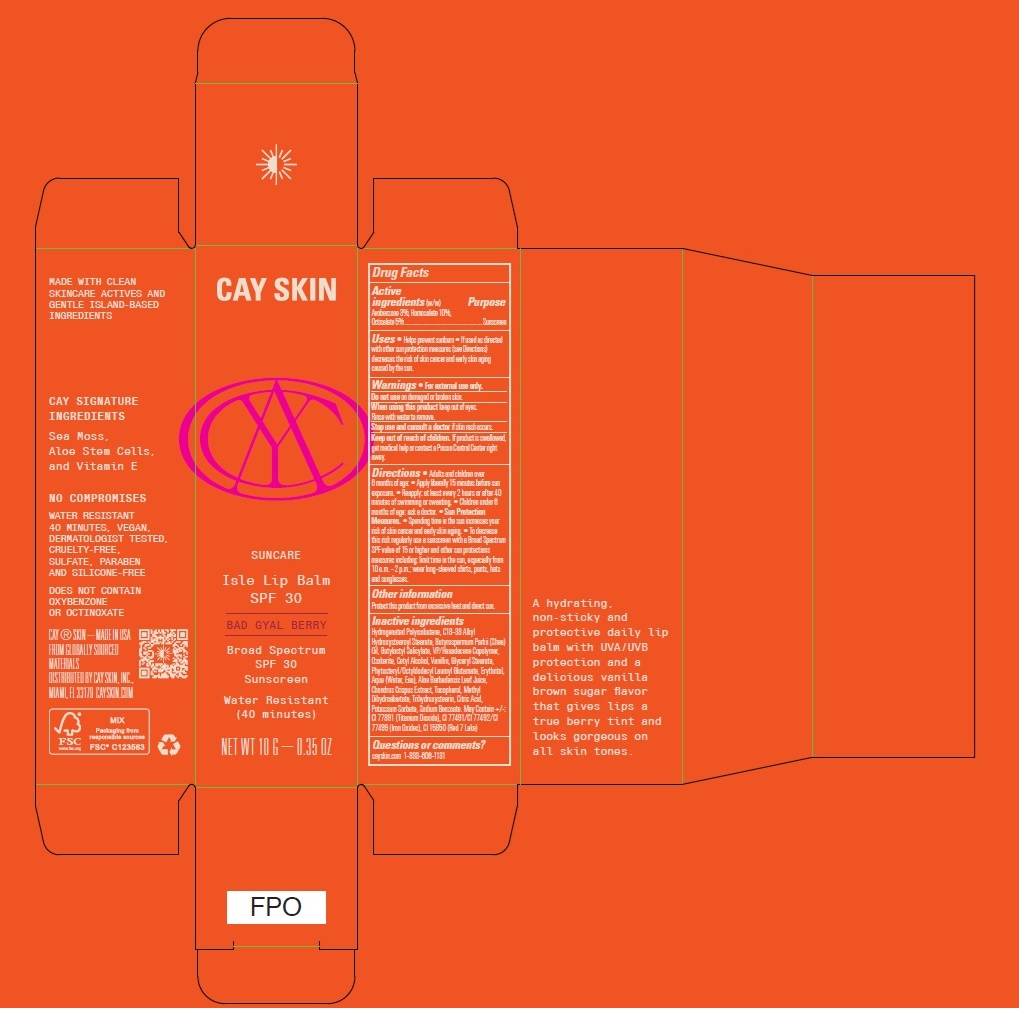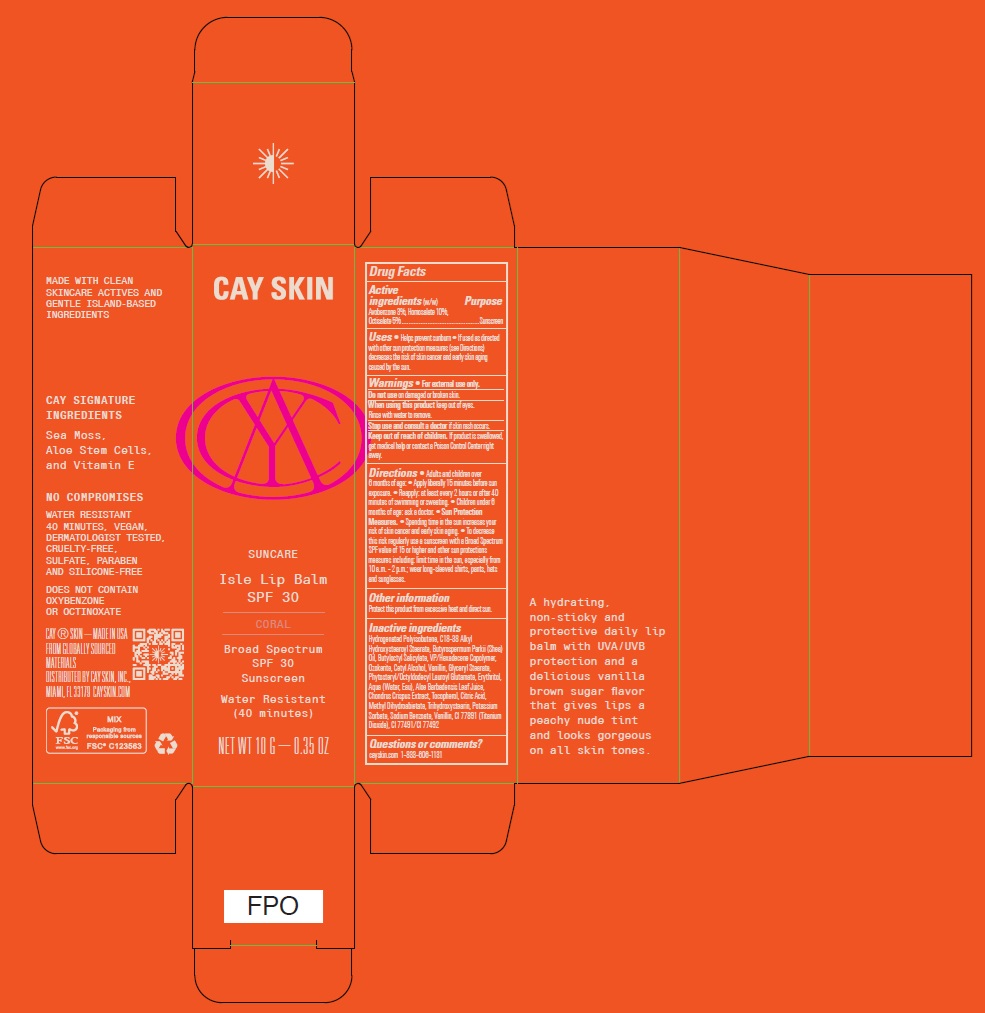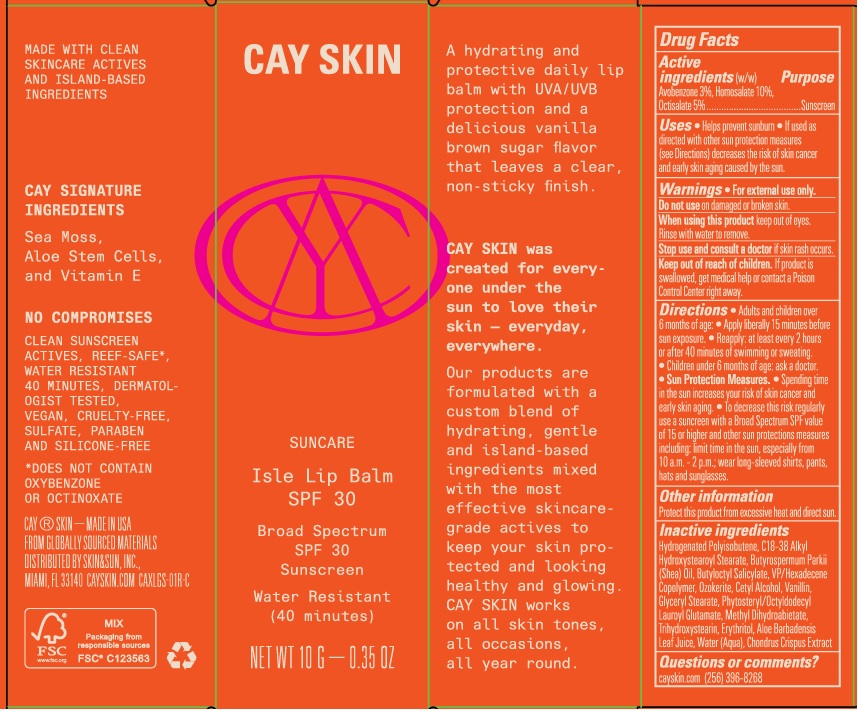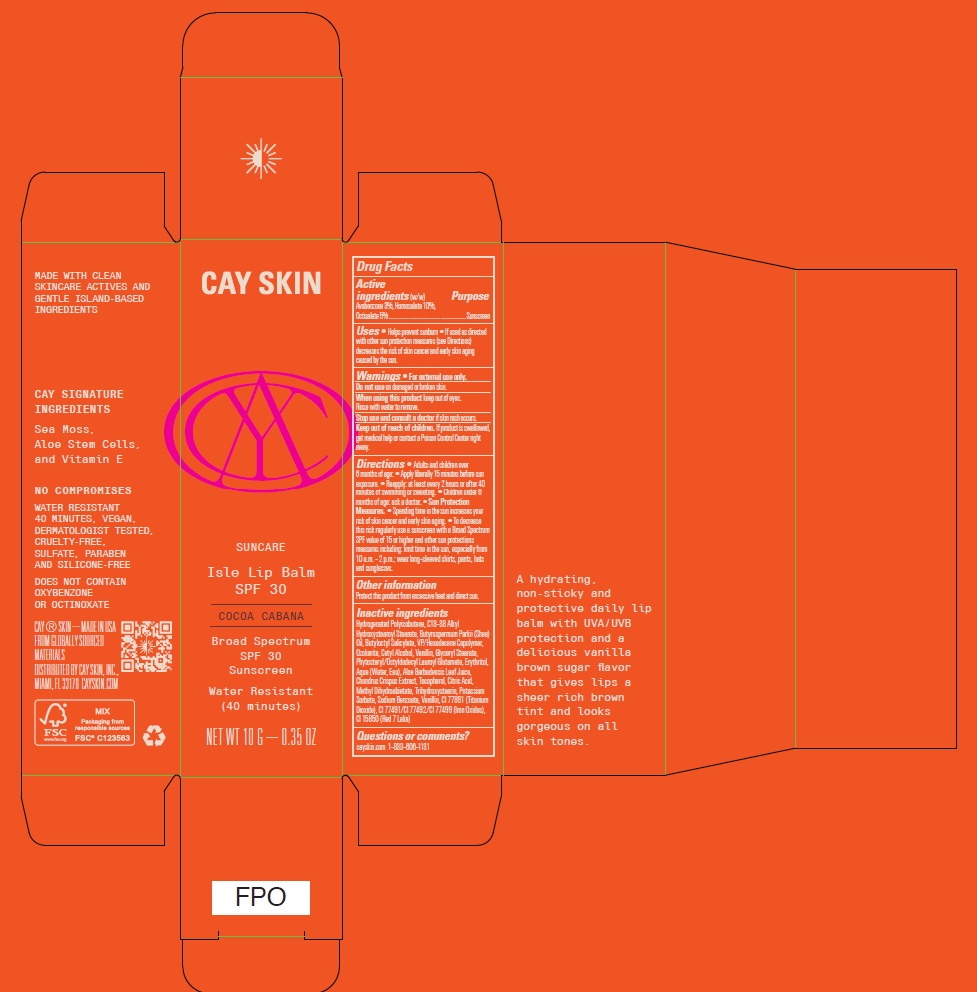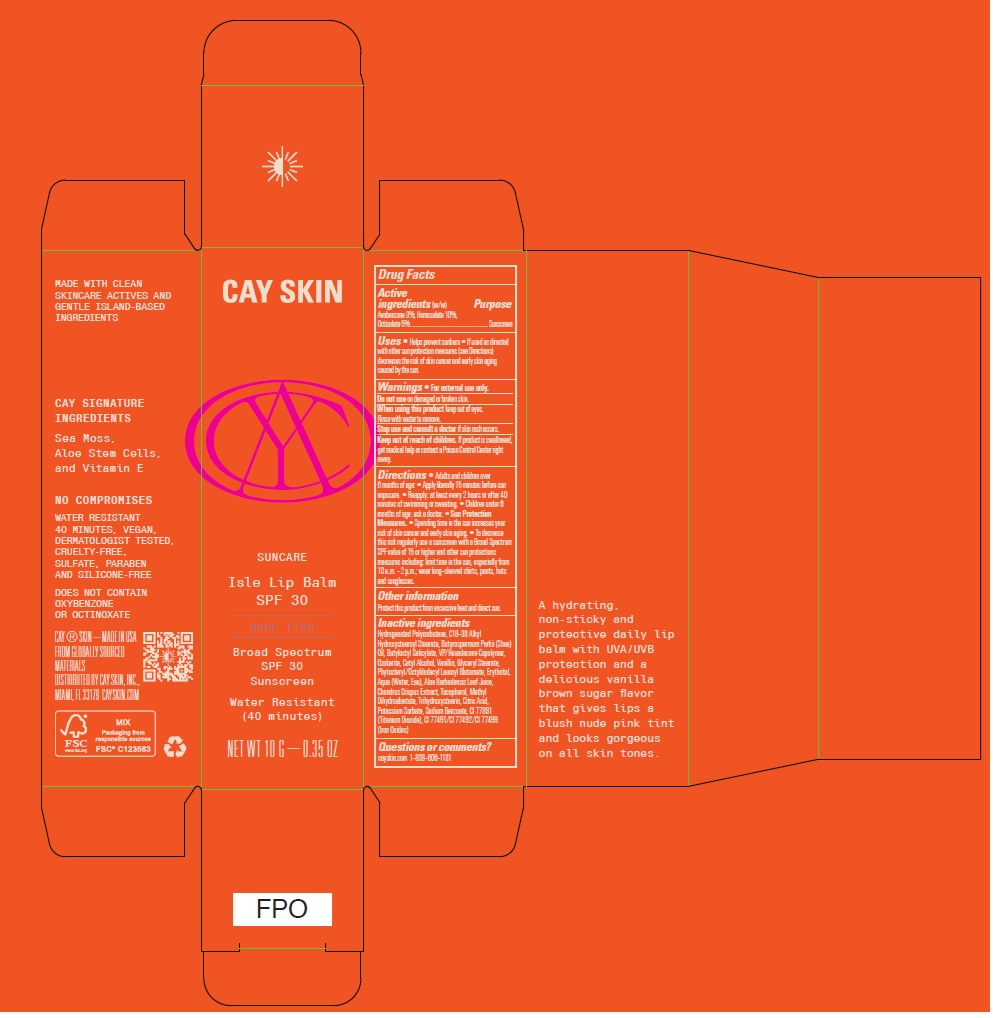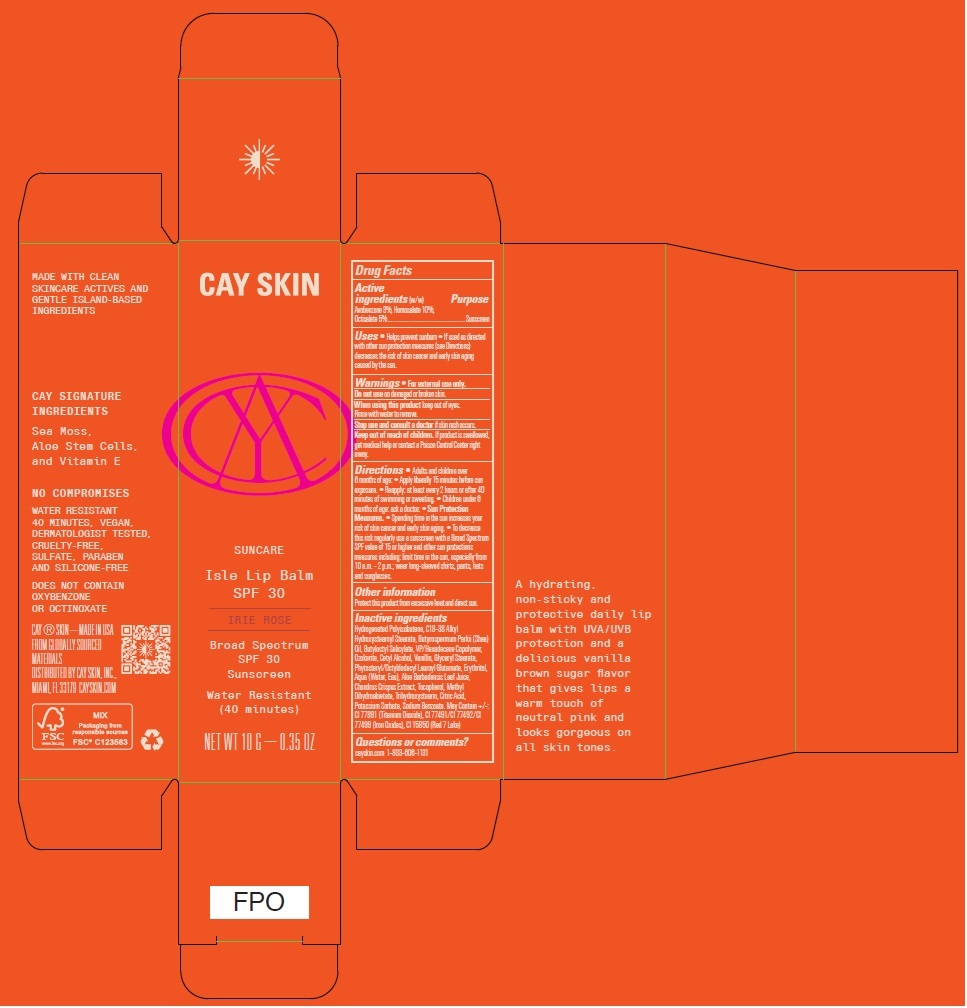 DRUG LABEL: Cay Skin Isle Lip Balm SPF 30 Coral
NDC: 82657-011 | Form: CREAM
Manufacturer: Cay Skin, Inc.
Category: otc | Type: HUMAN OTC DRUG LABEL
Date: 20250116

ACTIVE INGREDIENTS: AVOBENZONE 30 mg/1 g; OCTISALATE 50 mg/1 g; HOMOSALATE 100 mg/1 g
INACTIVE INGREDIENTS: POTASSIUM SORBATE; CI 77492; SODIUM BENZOATE; SHEANUT OIL; BUTYLOCTYL SALICYLATE; GLYCERYL MONOSTEARATE; ERYTHRITOL; CHONDRUS CRISPUS; CETYL ALCOHOL; CERESIN; HYDROGENATED POLYBUTENE (1300 MW); PHYTOSTERYL/OCTYLDODECYL LAUROYL GLUTAMATE; METHYL DIHYDROABIETATE; TRIHYDROXYSTEARIN; WATER; C18-38 ALKYL HYDROXYSTEAROYL STEARATE; VINYLPYRROLIDONE/HEXADECENE COPOLYMER; VANILLIN; ALOE VERA LEAF; TITANIUM DIOXIDE; TOCOPHEROL; CI 77491; CITRIC ACID MONOHYDRATE

Cay Skin Isle Lip Balm SPF 30

Active ingredients (w/w)

Avobenzone 3%, Homosalate 10%, Octisalate 5%

Purpose

Sunscreen

Uses

- Helps prevent sunburn
- If used as directed with other sun protection measures (see Directions) decreases the risk of skin cancer and early skin aging caused by the sun.

Warnings

For external use only.

Do not use

on damaged or broken skin.

When using this product

keep out of eyes. Rinse with water to remove.

Stop use and consult a doctor

if skin rash occurs.

Keep out of reach of children.

If product is swallowed, get medical help or contact a Poison Control Center right away.

Directions

- Adults and children over 6 months of age:
- Apply liberally 15 minutes before sun exposure.
- Reapply: at least every 2 hours or after 40 minutes of swimming or sweating.
- Children under 6 months of age: ask a doctor.
- Sun Protection Measures.
- Spending time in the sun increases your risk of skin cancer and early skin aging.
- To decrease this risk regularly use a sunscreen with a Broad Spectrum SPF value of 15 or higher and other sun protection measures including: limit time in the sun, especially from 10 a.m. - 2 p.m.; wear long-sleeved shirts, pants, hats and sunglasses.

Other information

Protect this product from excessive heat and direct sun.

Inactive ingredients

Hydrogenated Polyisobutene, C18-38 Alkyl Hydroxystearoyl Stearate, Butyrospermum Parkii (Shea) Oil, Butyloctyl Salicylate, VP/Hexadecene Copolymer, Ozokerite, Cetyl Alcohol, Vanillin, Glyceryl Stearate, Phytosteryl/Octyldodecyl Lauroyl Glutamate, Methyl Dihydroabietate, Trihydroxystearin, Erythritol, Aloe Barbadensis Leaf Juice, Water (Aqua), Chondrus Crispus Extract

Cocoa Cabana

Hydrogenated Polyisobutene, C18-38 Alkyl Hydroxystearoyl Stearate, Butyrospermum Parkii (Shea) Oil, Butyloctyl Salicylate, VP/Hexadecene Copolymer, Ozokerite, Cetyl Alcohol, Vanillin, Glyceryl Stearate, Phytosteryl/Octyldodecyl Lauroyl Glutamate, Erythritol, Aqua (Water, Eau), Aloe Barbadensis Leaf Juice, Chondrus Crispus Extract, Tocopherol, Citric Acid, Methyl Dihydroabietate, Trihydroxystearin, Potassium Sorbate, Sodium Benzoate, Vanillin, CI 77891 (Titanium Dioxide), CI 77491/CI 77492/CI 77499 (Iron Oxides), CI 15850 (Red 7 Lake)

Coral

Hydrogenated Polyisobutene, C18-38 Alkyl Hydroxystearoyl Stearate, Butyrospermum Parkii (Shea) Oil, Butyloctyl Salicylate, VP/Hexadecene Copolymer, Ozokerite, Cetyl Alcohol, Vanillin, Glyceryl Stearate, Phytosteryl/Octyldodecyl Lauroyl Glutamate, Erythritol, Aqua (Water, Eau), Aloe Barbadensis Leaf Juice, Chondrus Crispus Extract, Tocopherol, Citric Acid, Methyl Dihydroabietate, Trihydroxystearin, Potassium Sorbate, Sodium Benzoate, Vanillin, CI 77891 (Titanium Dioxide), CI 77491/CI 77492

Nude Ting

Hydrogenated Polyisobutene, C18-38 Alkyl Hydroxystearoyl Stearate, Butyrospermum Parkii (Shea) Oil, Butyloctyl Salicylate, VP/Hexadecene Copolymer, Ozokerite, Cetyl Alcohol, Vanillin, Glyceryl Stearate, Phytosteryl/Octyldodecyl Lauroyl Glutamate, Erythritol, Aqua (Water, Eau), Aloe Barbadensis Leaf Juice, Chondrus Crispus Extract, Tocopherol, Methyl Dihydroabietate, Trihydroxystearin, Citric Acid, Potassium Sorbate, Sodium Benzoate, CI 77891 (Titanium Dioxide), CI 77491/CI 77492/CI 77499 (Iron Oxides)

Irie Rose

Hydrogenated Polyisobutene, C18-38 Alkyl Hydroxystearoyl Stearate, Butyrospermum Parkii (Shea) Oil, Butyloctyl Salicylate, VP/Hexadecene Copolymer, Ozokerite, Cetyl Alcohol, Vanillin, Glyceryl Stearate, Phytosteryl/Octyldodecyl Lauroyl Glutamate, Erythritol, Aqua (Water, Eau), Aloe Barbadensis Leaf Juice, Chondrus Crispus Extract, Tocopherol, Methyl Dihydroabietate, Trihydroxystearin, Citric Acid, Potassium Sorbate, Sodium Benzoate. May Contain +/-: CI 77891 (Titanium Dioxide), CI 77491/CI 77492/CI 77499 (Iron Oxides), CI 15850 (Red 7 Lake)

Bad Gyal Berry

Hydrogenated Polyisobutene, C18-38 Alkyl Hydroxystearoyl Stearate, Butyrospermum Parkii (Shea) Oil, Butyloctyl Salicylate, VP/Hexadecene Copolymer, Ozokerite, Cetyl Alcohol, Vanillin, Glyceryl Stearate, Phytosteryl/Octyldodecyl Lauroyl Glutamate, Erythritol, Aqua (Water, Eau), Aloe Barbadensis Leaf Juice, Chondrus Crispus Extract, Tocopherol, Methyl Dihydroabietate, Trihydroxystearin, Citric Acid, Potassium Sorbate, Sodium Benzoate. May Contain +/-: CI 77891 (Titanium Dioxide), CI 77491/CI 77492/CI 77499 (Iron Oxides), CI 15850 (Red 7 Lake)

Questions or comments?

cayskin.com (256) 396-8268